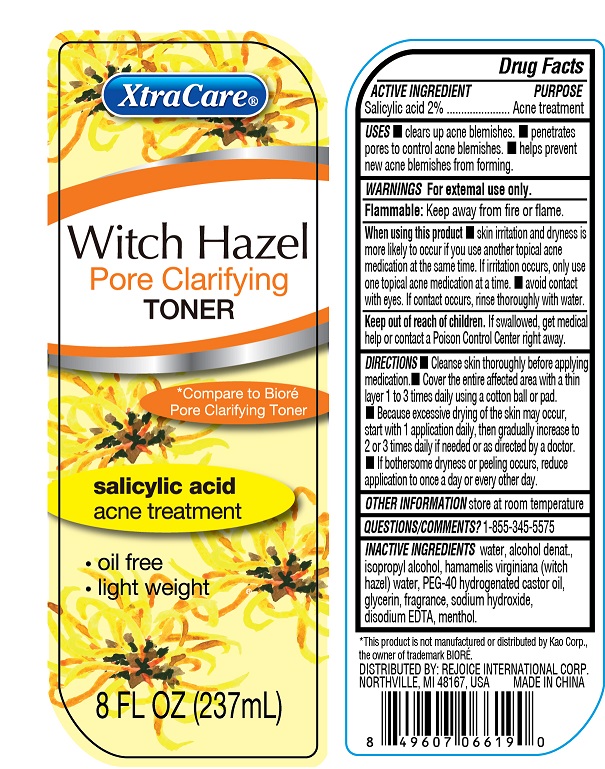 DRUG LABEL: Witch Hazel Pore Clarifying Toner
NDC: 57337-104 | Form: GEL
Manufacturer: Ningbo Rejoice International
Category: otc | Type: HUMAN OTC DRUG LABEL
Date: 20250213

ACTIVE INGREDIENTS: SALICYLIC ACID 20 mg/1 mL
INACTIVE INGREDIENTS: ISOPROPYL ALCOHOL; ALCOHOL; POLYOXYL 40 HYDROGENATED CASTOR OIL; WATER; GLYCERIN; DISODIUM EDTA-COPPER; WITCH HAZEL; MENTHOL; SODIUM HYDROXIDE

Witch Hazel Pore Clarifying Toner

Purpose

Acne treatment

Active Ingredient

Salicylic Acid 2%

Directions

- Cleanse skin thoroughly before applying medication.
- Cover the entire affected area with a thin layer 1 to 3 times daily using a cotton ball or pad.
- Because excessive drying of the skin may occur, start with 1 application daily, then gradually increase to 2 or 3 times daily if needed or as directed by a doctor.
- If bothersome dryness or peeling occurs, reduce application to once a day or every other day

Keep out of reach of children

If swallowed get medical help or contact a poison control center right away.

INACTIVE INGREDIENT

Water, alcohol denat., isopropyl alcohol, hamamelis virginiana (witch hazel) water, PEG-40 hydrogenated castor oil, glycerin, fragrance, sodium hydroxide, disodium EDTA, menthol

Warnings

For external use only

Flammable: Keep away from fire or flame

When using this product

- Skin irritation and dryness are more likely to occur if you use another topical acne medication at the same time. If irritation occurs, oinly use one topical acne medication at a time.
- Avoid contact with eyes. If contact occurs, rinse thoroughly with water

Uses

- Clears up acne blemishes
- Penetrates pores to control acne blemishes
- Helps prevent new acne blemishes from forming

Other Information

Store at room temperature

Questions / Comments?

1-855-345-5575